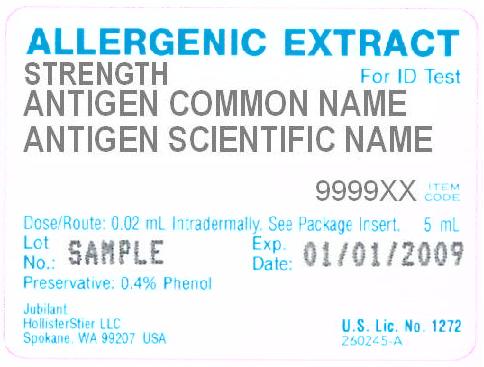 DRUG LABEL: Animal Allergens, AP Horse Hair and Dander
NDC: 65044-4857 | Form: INJECTION, SOLUTION
Manufacturer: Jubilant HollisterStier LLC
Category: other | Type: NON-STANDARDIZED ALLERGENIC LABEL
Date: 20180313

ACTIVE INGREDIENTS: EQUUS CABALLUS HAIR 0.0005 g/1 mL; EQUUS CABALLUS DANDER 0.0005 g/1 mL
INACTIVE INGREDIENTS: PHENOL; SODIUM CHLORIDE; SODIUM BICARBONATE; GLYCERIN

INSTRUCTIONS ALLERGENIC EXTRACTS FOR INTRADERMAL TESTING

WARNINGS

This product is intended for use only by licensed medical personnel experienced in administering allergenic extracts and trained to provide immediate emergency treatment in the event of a life-threatening reaction.

Allergenic extracts may potentially elicit a severe life-threatening systemic reaction, rarely resulting in death.7 Therefore, emergency measures and personnel trained in their use should be available immediately in the event of such a reaction. Patients should be instructed to recognize adverse reaction symptoms and cautioned to contact the physician's office if symptoms occur.

Scratch, prick or puncture test first. Test intradermally only to those antigens giving negative or questionable reactions on scratch, prick or puncture testing.

This product should never be injected intravenously.

Patients on non-selective beta blockers may be more reactive to allergens given for testing or treatment and may be unresponsive to the usual doses of epinephrine used to treat allergic reactions.6

Refer also to the WARNINGS, PRECAUTIONS, and ADVERSE REACTIONS Sections below for further discussion.

DESCRIPTION

Extracts for intradermal testing are supplied in sterile multi-dose vials containing, in addition to the extract allergens and antigens, 0.5% sodium chloride, 0.275% sodium bicarbonate, up to 2% glycerin, 2.5% glycerin for AP™ products, and, as preservative, 0.4% phenol. The strength of these extracts may be expressed in terms of:

1. Weight to Volume (w/v)
2. Protein Nitrogen Units/mL (PNU/mL)
3. Allergy Units/mL (AU/mL)
4. Bioequivalent Allergy Units/mL (BAU/mL)
5. Concentrate

- Weight to volume (w/v). For regular extracts this describes the extraction ratio, i.e., the amount of crude allergen added to the extracting fluid. A 1:10 extract, therefore, indicates that the solution contains the extracted material from one gram of raw material added to each 10 mL of extracting fluid. The amount and composition of extracted material will vary with the kind of antigen, the extracting fluid, duration of extraction, pH, temperature, and other variables. In contrast to this, AP™ (acetone precipitated) extracts, if present, are prepared by reconstituting dry allergenically active concentrates produced by a precipitation process from extracts of raw materials. For those AP™ extracts labeled on a weight per volume (w/v) basis, the strength designation indicates the dry weight of finished (acetone) precipitate per volume of reconstituting fluid. For example, 1:50 (w/v) means that each gram of dry precipitate obtained from the original extract is reconstituted in 50 mL of solution.
- Protein Nitrogen Units per mL (PNU/mL). One protein nitrogen unit represents 0.00001 mg phosphotungstic acid-precipitable protein nitrogen dissolved in one mL of antigen extract. The PNU content of extracts of the same antigen may vary according to the method of measuring the PNU. Thus, PNU contents of extracts from different manufacturers are not comparable unless the PNU method is known to be the same and reproducible from lot to lot. Also, the amount of protein nitrogen extracted from an antigen is influenced by the same variables as the weight to volume extract. Allergenic materials make up a variable proportion of the total protein of an extract.
- Allergy Units per mL (AU/mL). The potency of standardized AP™ and regular extracts labeled in Allergy Units (AU)/mL is determined by in vitro comparison to the reference standard established by the Center for Biologics Evaluation and Research (CBER) of the Food and Drug Administration.
- Bioequivalent Allergy Units per mL(BAU/mL). When originally licensed, the Reference Preparations for standardized extracts were arbitrarily assigned 100,000 Allergy Units (AU)/mL. Subsequently, quantitative skin testing by the ID50EAL method14 was used to determine that some Reference Preparations should be assigned 10,000 AU/mL, and others 100,000 AU/mL. To avoid possible confusion about this change in the method of allergy unit assignment, the nomenclature changed for standardized extracts whose allergy units are assigned based on quantitative skin testing, and are labeled in Bioequivalent Allergy Units (BAU)/mL. References labeled 10,000 BAU/mL can be diluted one to a half million fold, and references labeled 100,000 BAU/mL can be diluted one to 5 million fold and produce a sum of erythema diameter of 50 mm when Intradermal testing highly reactive subjects.
- Concentrate. Concentrate label terminology applies to allergenic extract mixtures, where the individual allergens being combined vary in strength or the designation of strength.

CLINICAL PHARMACOLOGY

Allergenic extracts for intradermal testing used according to the DOSAGE AND ADMINISTRATION Section, produce erythema or erythema and wheal reactions in patients with significant IgE-mediated sensitivity to the relevant allergen. This allergic inflammatory response, although not completely understood, is thought to begin with the reaction of antigen with IgE on the surface of basophils, or mast cells, which initiates a series of biochemical events resulting in the production of histamine, slow-reacting substance of anaphylaxis and other mediators. These, in turn, produce the immediate-type wheal and flare skin reaction.

INDICATIONS AND USAGE

Certain diagnostics carry labeling which states Allergenic Extract for Diagnostic Use Only. Data to support the therapeutic use of products labeled with this statement have not been established.15

In addition to a carefully taken history, the use of intradermal testing extracts is an accepted method in the diagnosis of allergenic conditions.1, 2, 3 When scratch, prick or puncture reactions are small, or if the patient gives a history of allergic symptoms to a substance but scratch, prick or puncture tests are inconclusive, intradermal tests may be indicated. However, ANTIGENS PRODUCING LARGE 3 TO 4+ SCRATCH, PRICK OR PUNCTURE TESTS SHOULD NOT BE TESTED INTRADERMALLY.

Extracts of all allergens do not produce equivalent results in intradermal testing. The intensity of the skin reaction produced will be determined by two factors: the degree of sensitivity of the patient and the nature of the antigenic extract applied. In general, pollen extracts produce whealing reactions, whereas other inhalants produce erythematous reactions with wheals less often. Skin tests to foods seldom produce whealing reactions except for infrequent instances of severe sensitivity to fish, nuts or spices, and rarely other foods.

CONTRAINDICATIONS

There are no known absolute contraindications to allergy skin testing. Patients with cardiovascular diseases or pulmonary diseases such as symptomatic asthma, and/or who are receiving cardiovascular drugs such as beta blockers, may be at higher risk for severe adverse reactions. These patients may also be more refractory to the normal anaphylaxis treatment regime.

WARNINGS

Scratch, prick or puncture test first. Test intradermally only to those antigens giving negative or questionable reactions on scratch, prick or puncture testing. Excessively large local reactions or systemic reactions are more likely to occur if the patient is skin tested shortly after exposure to large amounts of antigen to which he or she is sensitive. Therefore, use caution when applying pollen tests to patients during their active pollen season, or after an exposure to inhalant allergens that produce symptoms. Refer to boxed WARNINGS Section.

PRECAUTIONS

1. General

It is recommended that disposable syringes and needles are used for intradermal tests to prevent the possibility of accidental transfer of serum hepatitis and other infectious agents from one person to another. Always have injectable epinephrine and a tourniquet available when tests are being made. (See ADVERSE REACTION Section.) Patients should be observed in the office for 30 to 45 minutes after each set of intradermal tests and instructed to return to the office promptly if symptoms of an allergic reaction or shock occur. In order to avoid darkening and possible precipitation, do not dilute the following extracts with solutions containing phenol: Privet pollen and food extracts of White Potato, Corn, Oat, Rye, and Wheat. Injections of such extracts discolored by reaction with phenol may produce lasting tattoo-like discoloration of the skin.

2. Information for Patients

Patients should be instructed in the recognition of adverse reactions to diagnostic testing. Patients should be made to understand the importance of a 30 to 45 minute observation period and be warned to return to the office promptly if symptoms occur after leaving.

3. Carcinogenesis, Mutagensis, Impairment of Fertility

Long-term studies in animals have not been conducted with allergenic extracts to determine their potential for carcinogenicity, mutagenicity or impairment of fertility.

4. Pregnancy

4,5 Animal reproduction studies have not been conducted with allergenic extracts. It is also not known whether allergenic extracts can cause fetal harm when administered to a pregnant woman or can affect reproduction capacity. Allergenic extracts should be given to a pregnant woman only if clearly needed.

5. Nursing Mothers

There are no current studies on secretion of the allergenic extract components in human milk or effect on the nursing infant. Because many drugs are excreted in human milk, caution should be exercised when allergenic extracts are administered to a nursing woman.

6. Drug Interactions

Patients on non-selective beta blockers may be more reactive to allergens given for testing or treatment and may be unresponsive to the usual doses of epinephrine used to treat allergic reactions.6
Certain medications may lessen the skin test wheal and erythema responses elicited by allergens and histamine for varying time periods. Conventional antihistamines should be discontinued at least 5 days before skin testing. Long acting antihistamines should be discontinued for at least 3 weeks prior to skin testing.10Topical steroids should be discontinued at the skin test site for at least 2-3 weeks before skin testing. 10, 11 Tricyclic antidepressants such as Doxepin should be withheld for at least 7 days before skin testing.12Topical local anesthetics may suppress the flare responses and should be avoided in skin test sites. 13

7. Geriatric Use

Skin test wheal size decreases with age. The decrease in allergeninduced skin test reaction parallels that to histamine; therefore, appropriate positive skin test controls should always be performed.1

8. Pediatric Use

Wheal sizes in response to allergen skin testing can be smaller in infants than in adults. The skin response to histamine parallels that for allergens; therefore, appropriate postitive control skin tests should always be performed.1

ADVERSE REACTIONS

1. Local Reactions

Large, persistent local reactions or minor exacerbations of the patient's allergic symptoms may be treated by local cold applications and/or the use of oral antihistamines, but they should be considered a warning of possible severe systemic reactions.

2. Systemic Reactions
With careful attention to dosage and administration, such reactions occur infrequently, but it must be remembered that allergenic extracts are highly potent in sensitive individuals and OVERDOSE could result in anaphylactic symptoms. Therefore, it is imperative that physicians administering allergenic extracts understand and be prepared for the treatment of severe reactions. Adverse reaction frequency data for allergenic extract administration for testing and treatment show that risk is low.7, 8 It cannot be overemphasized that, under certain unpredictable combinations of circumstances, anaphylactic shock is a possibility. Other possible systemic reaction symptoms, in varying degrees of severity, are fainting, pallor, bradycardia, hypotension, angioedema, cough, wheezing, conjunctivitis, rhinitis and urticaria. If a systemic or anaphylactic reaction does occur, apply a tourniquet above the site of injection, if tests are performed on the arms, and inject the 1:1000 epinephrine-hydrochloride intramuscularly or subcutaneously into the opposite arm. Loosen the tourniquet at least every 10 minutes. Do not obstruct arterial blood flow with the tourniquet.

EPINEPHRINE:
ADULT DOSAGE: 0.3 to 0.5 mL should be injected. Repeat in 5 to 10 minutes if necessary.
PEDIATRIC DOSAGE: The usual initial dose is 0.01 mg (mL) per kg body weight or 0.3 mg (mL) per square meter of body surface area. Suggested dosage for infants to 2 years of age is 0.05 mL to 0.1 mL; for children 2 to 6 years, 0.15 mL; and children 6 to 12 years, 0.2 mL. Single pediatric doses should not exceed 0.3 mg (mL). Doses may be repeated as frequently as every 20 minutes, depending on the severity of the condition and the response of the patient. After administration of epinephrine, profound shock or vasomotor collapse should be treated with intravenous fluids, and possibly vasoactive drugs. Oxygen should be given by mask. Intravenous antihistamine, theophylline or adrenal corticosteroids may be used if necessary after adequate epinephrine and circulatory support have been given. Emergency resuscitation measures and personnel trained in their use should be available immediately in the event of a serious systemic or anaphylactic reaction not responsive to the above measures. [Ref. J. Allergy Clin. Immunol. 77 (2): 271-273, 1986]. Rarely are all of the above measures necessary; the tourniquet and epinephrine usually produce prompt responses. However, the physician should be prepared in advance for all contingencies. Promptness in beginning emergency treatment measures is of utmost importance.

3. Adverse Event Reporting
Report all adverse events to Jubilant HollisterStier LLC Customer Technical Services Department at 1 (800) 992-1120. A voluntary adverse event reporting system for health professionals is available through the FDA MEDWATCH program. Preprinted forms (FDA Form 3500) are available from the FDA by calling 1 (800) FDA-1088. Completed forms should be mailed to MEDWATCH, 5600 Fisher Lane, Rockville, MD 20852-9787 or Fax to: 1 (800) FDA-0178.

OVERDOSE SECTION

See ADVERSE REACTIONS Section.

DOSAGE AND ADMINISTRATION

1. General

Parenteral Drug Products should be inspected visually for particulate matter and discoloration prior to administration, whenever solution and container permit.
2. Intradermal Testing Methods
Cleanse the rubber stopper of the vial with liquid antiseptic before withdrawing extract. A sterile tuberculin syringe with 26-gauge, short-bevel needle should be used for the injection. The anterior surface of the upper and lower arm is preferable for testing. Cleanse the skin with soap and water or wash with alcohol or other antiseptic. Introduce the needle between the superficial layers of the skin and inject 0.02 mL of the extract. Test sites should be at least 2.5 cm apart, and no more than 10 to 20 antigens should be introduced at one time. This group can be followed with additional groups of 10, providing the reactions are not numerous or strong. The same amount of extract should be injected in each site for proper comparison. It is advisable to avoid testing with more than one allergen in the same group in each series, i.e., nuts, fish, epidermals, etc. A site should be injected with 0.02 mL of the control solution. All skin tests should be validated by appropriate positive control tests (e.g., histamine) and negative control tests [e.g., Glycerin, Albumin Saline with Phenol (0.4%), or Buffered Saline with Phenol (0.4%)]. The negative control test should be the same material as is used as a diluting fluid in the tested extracts. Diluting fluid is used in the same way as an active test extract. False positive reactions are sometimes encountered in intradermal testing, and the possibility of irritation reactions should always be taken into consideration. In cases where the patient is known to be quite sensitive, screen testing by scratch, prick or puncture method is recommended, and intradermal testing should be done with caution. The intradermal strength supplied is usually safe for testing patients presenting negative scratch, prick or puncture test reactions. It is recommended that a 1:10 dilution of the stock intradermal strength be used in preliminary testing of patients not previously screened by scratch, prick or puncture tests.
3. Use of Antigen Mixes
The use of complicated mixes of unrelated pollens for testing is not recommended since in the case of a positive reaction it does not indicate which pollen(s) are responsible, and in the case of a negative reaction, it fails to indicate whether the individual pollens at full concentration would give a positive reaction.
4. Reading Skin Test Reactions
A positive reaction consists of an urticarial wheal with surrounding erythema (resembling somewhat a mosquito bite reaction) larger than the control site. The smallest reaction considered positive is erythema with a central papule at least 5 mm in diameter. In some instances with no reaction at the control site, erythema may be considered an indication of sensitivity. In general, the size of wheal and erythema response correlates directly with the patient's sensitivity to that allergen.
Standardized Products
(a) Mites: The skin test concentrations of 30 AU/mL and 300 AU/mL in multiple dose vials are used for intradermal testing.
Intradermal skin test results in selected highly sensitive subjects are presented for reference purposes:

AU/mL that Elicited ∑E = 50 mm
Allergen | Number of Persons | Mean | 2 Std. Dev. Range
D. farinae | 12 | 0.0609 | 0.0015-2.6016
D. pteronyssinus | 12 | 0.333 | 0.0003-4.0077

Intradermal extracts should be used as follows:
(1) Patients with a negative scratch, prick or puncture test: Patients who do not react to a valid scratch, prick or puncture test should be tested intradermally with 0.02 to 0.05 mL of a 30 AU/mL extract solution. If this test is negative, a second intradermal test may be performed using a 300 AU/mL extract solution. The negative control used with this latter dilution should contain 0.5% glycerin.
(2) Patients tested only by the intradermal method: Patients suspected of being highly allergic should be tested with 0.02 to 0.05 mL of a solution containing 0.03 AU/mL. A negative test should be followed by repeat tests using progressively stronger concentrations until the maximum recommended strength of 300 AU/mL is reached. The negative control used with this latter dilution should contain 0.5% glycerin.
(b) Cat Hair and Cat Pelt: Intradermal endpoint titration (IET) tests were completed with Cat Pelt extract using 15 subjects to determine the mean concentration required to produce a ∑E of 50 (D50) mm.That concentration contained 0.042 BAU/mL (range 0.002 to 0.890 BAU/mL).
IET tests were completed with Cat Hair extract using 15 subjects to determine the mean concentration required to produce a ∑E of 50 mm (D50). That concentration contained 0.049 BAU/mL (range 0.006 to 0.661 BAU/mL).
Intradermal extract should be used as follows:
Intradermal Tests should be done only on patients with a negative prick or puncture test. Patients who do not react to a valid prick or puncture test should be tested intradermally with 0.02 to 0.05 mL of a 100 BAU/mL extract solution. If this test is negative, a second intradermal test may be performed using a 1,000 BAU/mL extract solution. If the intradermal dilutions were prepared from glycerinated concentrate, the negative control used with this latter dilution should contain 5% glycerin.
Standardized Cat Hair and Cat Pelt products are not interchangeable with each other or any other cat products including those labeled AU/mL.
(c) Ragweed pollen (Short Ragweed or Giant and Short Ragweed Mixture) Antigen E Assayed: The intradermal strength for Short Ragweed extract is usually 500 PNU, which by calculation contains approximately 0.7 to 3 units of Antigen E/mL. For Giant and Short Ragweed mix the suggested intradermal strength is 500 PNU, which by calculation contains 0.4 to 1.5 units of Antigen E/mL. These strengths are usually safe for testing patients previously having negative scratch, prick or puncture test reactions. A 1:10 dilution of the stock intradermal strength should be used in preliminary testing of patients not previously screened by scratch, prick, or puncture tests. A study of ragweed sensitive patients9 indicates that intradermal tests, using 0.05 mL of extract, produce positive reactions (1+ to 2+) at Antigen E concentrations of from 2.7x10 -1 to 2.7x10 -6 units per mL. The equivalent PNU range was 100 to 0.001 PNU per mL. Skin tests are graded in terms of the wheal and erythema response noted at 15 minutes. Wheal and erythema size may be recorded by actual measurement of the extent of both responses.

5. Geriatric Use

The dose is the same in patients of all age groups. Because the wheal size in response to allergen skin testing decreases with age, appropriate histamine positive control skin tests must be performed.1

6. Pediatric Use

The dose is the same in patients of all age groups. Wheal size in response to allergen skin testing can be smaller in infants than in adults. Appropriate histamine positive control skin tests must be performed.1

Refer to the following table to determine the skin test sensitivity grade. The corresponding ∑E (sum of the longest diameter and the mid-point orthogonal diameters of erythema) is also presented.

Grade | Erythema mm | Papule or Wheal mm | Coresponding mm ∑E
0 | <5 | <5 | <10
± | 5-10 | 5-10 | 10-20
1+ | 11-20 | 5-10 | 20-40
2+ | 21-30 | 5-10 | 40-60
3+ | 31-40 | 10-15 (a) | 60-80
4+ | >40 | >15 (b) | > 80

a or with pseudopods

b or with many pseudopods

A positive skin reaction to any allergen must be interpreted in light of the patient’s history of symptoms, time of year, known exposures, and eating habits.
THE SKIN TESTS ARE IN NO WAY A SUBSTITUTE FOR A CAREFUL ALLERGENIC HISTORY; RATHER, THEY SERVE AS ADDITIONAL INFORMATION TO AID IN IDENTIFYING CAUSATIVE ALLERGENS IN PATIENTS WITH ALLERGIC DISORDERS.

HOW SUPPLIED

Most allergens are available in multiple dose 5 mL vials at PNU, w/v, some mixes as Concentrate, Standardized Mite products at AU/mL (30 AU/mL and 300 AU/mL each species), or Standardized Grass products at BAU/mL [100 BAU/mL and 1,000 BAU/mL (Bermuda 100 BAU/mL only)]. Product labels state vials are for intradermal testing and list strengths.

STORAGE

The expiration date of the diagnostic extracts is listed on the container label. The extract should be stored at 2° to 8°C, and kept at this temperature range during office use.

LIMITED WARRANTY

A number of factors beyond our control could reduce the efficacy of this product or even result in an ill effect following its use. These include storage and handling of the product after it leaves our hands, diagnosis, dosage, method of administration and biological differences in individual patients. Because of these factors, it is important that this product be stored properly, and that the directions be followed carefully during use. No warranty, express or implied, including any warranty of merchantability or fitness, is made. Representatives of the Company are not authorized to vary the terms or the contents of any printed labeling, including the package insert, for this product except by printed notice from the Company’s headquarters. The prescriber and user of this product must accept the terms hereof.

REFERENCES

1. Middleton, Elliott, Jr., C. E. Reed, E. F. Ellis (ed.) Allergy Principles and Practice. Vol. 1, C. V. Mosby. 1978.

2. Sheldon, J. M., R. C. Lovell, K. P. Mathews. A Manual of Clinical Allergy. W. B. Saunders, 1967.
3. Tuft, L., H. L. Mueller. Allergy in Children. W. B. Saunders. 1979.
4. DuBuske, L.M., C.J. Ling and A.L. Sheffer. Special problems regarding allergen immunotherapy. Immunol. Allergy. Clin. North Am. (USA). 12(1): 145-175, 1992.
5. Weinstein, A. M., D. B. Dubin, W. K. Podleski, L. L. Spector, R. S. Farr. Asthma and pregnancy. JAMA. 134(11): 1161-1165, 1979.
6. Jacobs, Robert L., Goeffrey W. Rake, Jr., et al. Potentiated anaphylaxis in patients with drug-induced beta-adrenergic blockade. J. Allergy Clin. Immunol. 68(2): 125-127, August 1981.
7. Lockey, Richard F., Linda M. Benedict, Paul C. Turkeltaub, Samuel C. Bukantz. Fatalities from immunotherapy (IT) and skin testing (ST). J. Allergy Clin. Immunol. 79(4): 660-677, 1987.
8. Turkeltaub, Paul C., Peter J. Gergen. The risk of adverse reactions from percutaneous prick-puncture allergen skin testing, venipuncture, and body measurements: Data from the second National Health and Nutrition Examination Survey 1976-80 (NHANES II). J. Allergy Clin. Immunol. 84(6): 886-890, Dec. 1989.
9. Norman, P. S., L. M. Lichtenstein, K. Ishizaka. Diagnostic tests in ragweed hay fever. J. Allergy Clin. Immunol. 52(4): 212-224, 1973.
10. Pipkorn, Ulf. Pharmacological influence of anti-allergic medication on In Vivo allergen testing. Allergy. 43: 81-86, 1988.
11. Andersson, M., U. Pipkorn. Inhibition of the dermal immediate allergic reaction through prolonged treatment with topical glucocorticosteroids. J. Allergy Clin. Immunol. 79(2): 345-349, February 1987.
12. Rao, Kamineni S., et al. Duration of suppressive effect of tricyclic anti-depressants on histamine induced wheal and flare reactions on human skin. J. Allergy Clin. Immunol. 82: 752-757, November 1988.
13. Pipkorn, Ulf, M. Andersson. Topical dermal anesthesia inhibits the flare but not the wheal response to allergen and histamine in the skin prick test. Clinical Allergy. 17: 307-311, 1987.
14. Turkeltaub, Paul C., C. Rastogi Suresh, Harold Baer. Office of Biologics Research and Review skin test method for evaluation of subject sensitivity to standardized allergenic extracts and for assignment of allergy units to reference preparations using the ID50EAL method (Intradermal Dilution for 50 mm Sum of Erythema Determines the Allergy Unit). Methods of the Allergenic Products Branch Office of Biologics Research and Review, FDA, Bethesda, MD 20892. Revised May 9, 1986.
15. Food and Drug Administration. Biological products; Allergenic extracts classified in Category IIIB; Final order; Revocation of licenses. Federal Register. 59(220):59228ff, November 16, 1994.
16. Griffith, I.J., Pollock, D.G. Klapper, B.L. Rogers, A.K. Nault., Sequence Polymorphism of Amb a I and Amb a II, the Major Allergens in Ambrosia artemisiifolia (Short Ragweed). Int. Arch. Allergy Apply. Immunol., 96: 296-304, 1991.